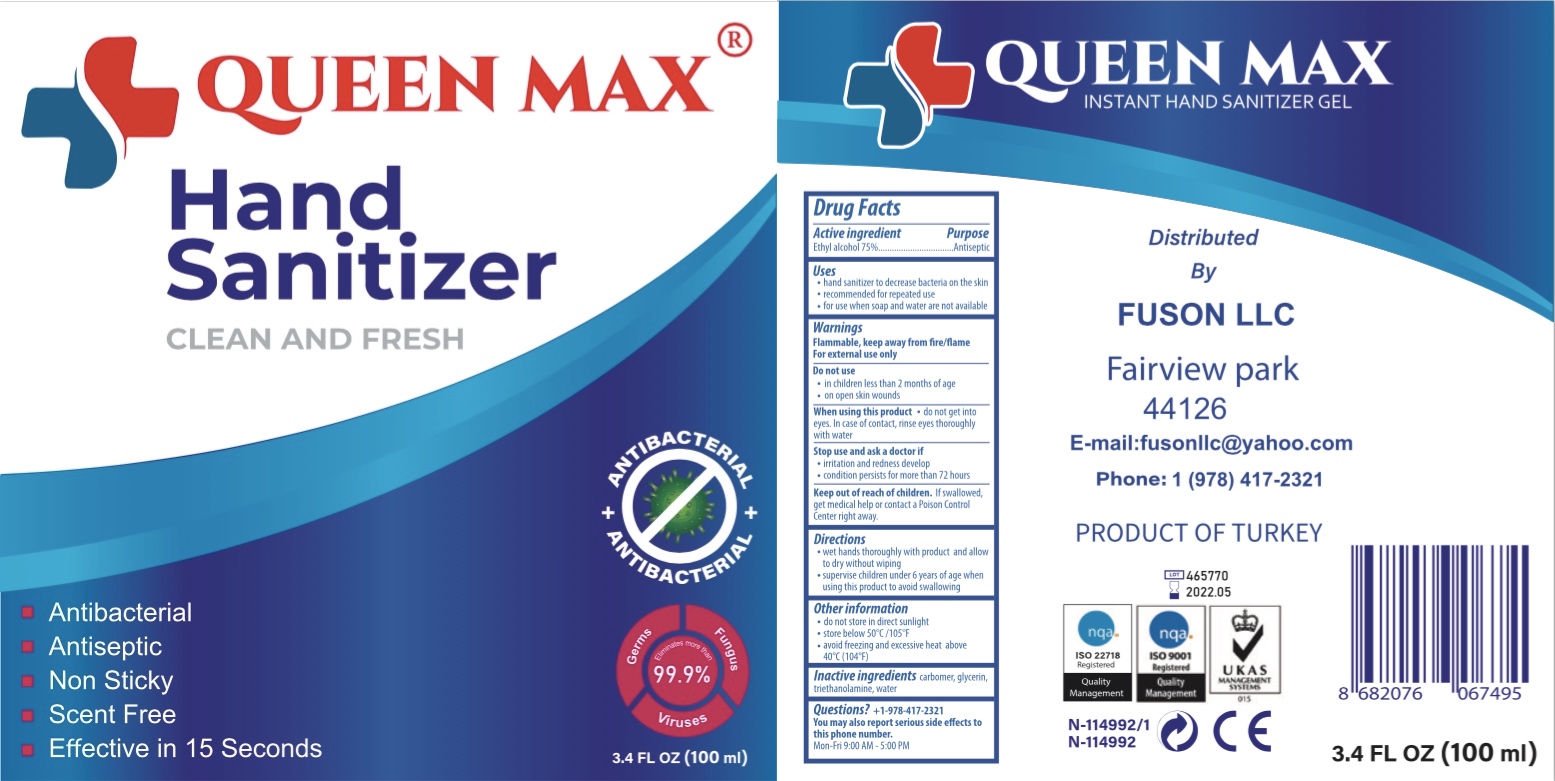 DRUG LABEL: QUEEN MAX
NDC: 77550-124 | Form: GEL
Manufacturer: MAQAS GROUP GAYRIMENKUL TURIZM SANAYI VE TICARET LIMITED SIRKETI
Category: otc | Type: HUMAN OTC DRUG LABEL
Date: 20200606

ACTIVE INGREDIENTS: ALCOHOL 75 mL/100 mL
INACTIVE INGREDIENTS: TROLAMINE; CARBOMER 940; GLYCERIN; WATER

MAQAS-FUSON QEEN MAX SANITIZER GEL

Active Ingredient(s)

Alcohol 75% v/v. Purpose: Antiseptic

Purpose

Antiseptic, Hand Sanitizer

Use

Hand Sanitizer to help reduce bacteria that potentially can cause disease. For use when soap and water are not available.

Warnings

For external use only. Flammable. Keep away from heat or flame

Do not use

- in children less than 2 months of age
- on open skin wounds

When using this product keep out of eyes, ears, and mouth. In case of contact with eyes, rinse eyes thoroughly with water.
Stop use and ask a doctor if irritation or rash occurs. These may be signs of a serious condition.
Keep out of reach of children. If swallowed, get medical help or contact a Poison Control Center right away.

Stop use and ask a doctor if irritation or rash occurs. These may be signs of a serious condition.

Keep out of reach of children. If swallowed, get medical help or contact a Poison Control Center right away.

Directions

- Wet hands thoroughly with product and allow to dry without wiping.
- Supervise children under 6 years of age when using this product to avoid swallowing.

Other information

- do not store in direct sunlight
- Store below 50C/105F
- Avoid freezing and excessive heat above 40C (104F)

Inactive ingredients

carbomer, glycerin, triethanolamine, water

Package Label - Principal Display Panel

100 mL NDC: 77550-124-10